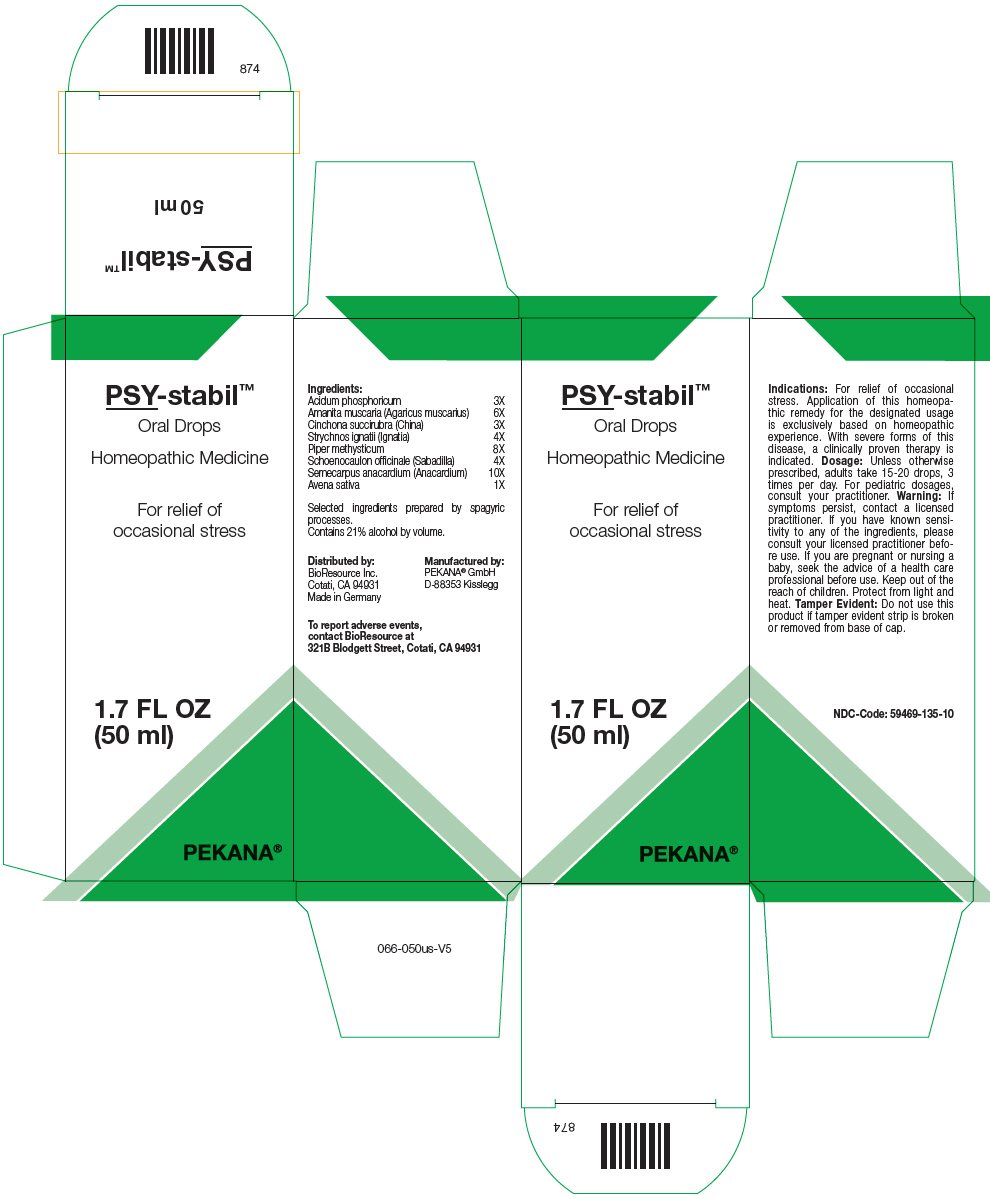 DRUG LABEL: PSY-stabil
NDC: 59469-135 | Form: SOLUTION/ DROPS
Manufacturer: PEKANA Naturheilmittel GmbH
Category: homeopathic | Type: HUMAN OTC DRUG LABEL
Date: 20221219

ACTIVE INGREDIENTS: Phosphoric Acid 3 [hp_X]/50 mL; Amanita muscaria Fruiting Body 6 [hp_X]/50 mL; Semecarpus anacardium Fruit 10 [hp_X]/50 mL; Avena sativa Flowering Top 1 [hp_X]/50 mL; Cinchona officinalis Bark 3 [hp_X]/50 mL; Strychnos ignatii Seed 4 [hp_X]/50 mL; Schoenocaulon officinale Seed 4 [hp_X]/50 mL; MACROPIPER METHYSTICUM ROOT 8 [hp_X]/50 mL
INACTIVE INGREDIENTS: Water; Alcohol

PSY-stabil™

ACTIVE INGREDIENT

Ingredients:
Acidum phosphoricum | 3X
Amanita muscaria (Agaricus muscarius) | 6X
Cinchona succirubra (China) | 3X
Strychnos ignatii (Ignatia) | 4X
Piper methysticum | 8X
Schoenocaulon officinale (Sabadilla) | 4X
Semecarpus anacardium (Anacardium) | 10X
Avena sativa | 1X

Selected ingredients prepared by spagyric processes.

INACTIVE INGREDIENT

Contains 21% alcohol by volume.

Indications

PURPOSE

For relief of occasional stress. Application of this homeopathic remedy for the designated usage is exclusively based on homeopathic experience. With severe forms of this disease, a clinically proven therapy is indicated.

Dosage

Unless otherwise prescribed, adults take 15-20 drops, 3 times per day. For pediatric dosages, consult your practitioner.

Warning

If symptoms persist, contact a licensed practitioner. If you have known sensitivity to any of the ingredients, please consult your licensed practitioner before use. If you are pregnant or nursing a baby, seek the advice of a health care professional before use.

Keep out of the reach of children.

STORAGE AND HANDLING

Protect from light and heat.

Tamper Evident

Do not use this product if tamper evident strip is broken or removed from base of cap.

QUESTIONS

To report adverse events, contact BioResource at 321B Blodgett Street, Cotati, CA 94931

Distributed by:
BioResource Inc.
Cotati, CA 94931

Manufactured by:
PEKANA® GmbH
D-88353 Kisslegg

PRINCIPAL DISPLAY PANEL - 50 ml Bottle Box

PSY-stabil™
Oral Drops

Homeopathic Medicine

For relief of
occasional stress

1.7 FL OZ
(50 ml)

PEKANA®